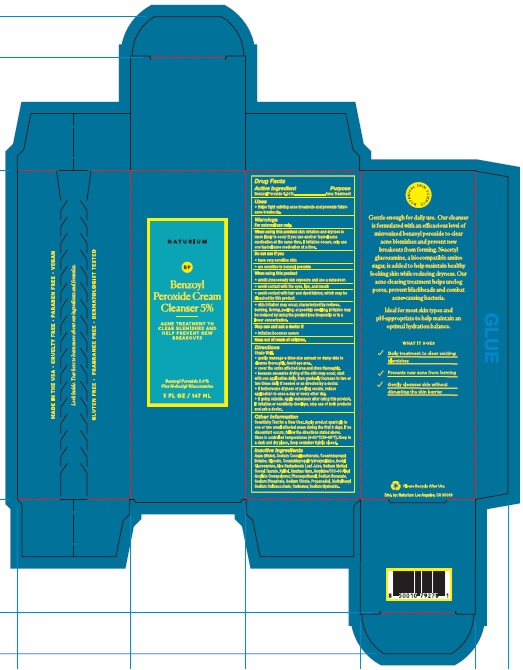 DRUG LABEL: Naturium Benzoyl Peroxide Cleanser 5%
NDC: 76354-123 | Form: CREAM
Manufacturer: e.l.f. Cosmetics, Inc
Category: otc | Type: HUMAN OTC DRUG LABEL
Date: 20251107

ACTIVE INGREDIENTS: BENZOYL PEROXIDE 50 mg/1 mL
INACTIVE INGREDIENTS: SODIUM HYDROXIDE; WATER; CARBOMER HOMOPOLYMER, UNSPECIFIED TYPE; SODIUM COCOYL ISETHIONATE; ALOE VERA LEAF; XYLITOL; XANTHAN GUM; CARBOMER INTERPOLYMER TYPE A (55000 CPS); PHENOXYETHANOL; SODIUM BENZOATE; PROPANEDIOL; COCAMIDOPROPYL BETAINE; GLYCERIN; N-ACETYLGLUCOSAMINE; SODIUM METHYL COCOYL TAURATE; SODIUM PHOSPHATE; COCAMIDOPROPYL HYDROXYSULTAINE; SODIUM CITRATE; DOCUSATE SODIUM

Naturium Benzoyl Peroxide Cream Cleanser 5%

Active Ingredient

Benzoyl Peroxide 5.00%

Purpose

Acne Treatment

Uses

- Helps fight existing acne breakouts and prevents future acne breakouts.

Warnings

For external use only.

When using this product

- skin irritation and dryness is more likely to occur if you use another topical acne medication at the same time. If irritation occurs, only use one topical acne medication at a time.
- avoid unnecessary sun exposure and use a sunscreen
- avoid contact with the eyes, lips, and mouth
- avoid contact with hair and dyed fabrics, which may be bleached by this product
- skin irritation may occur, characterized by redness, burning, itching, peeling, or possibly swelling. Irritation may be reduced by using the product less frequently or in a lower concentration.

Do not use if you

- have very sensitive skin
- are sensitive to benzoyl peroxide

Stop use and ask a doctor if

- irritation becomes severe

Keep out of reach of children.

Directions

Shake Well.

- gently massage a dime size amount on damp skin to cleanse thoroughly. Avoid eye area.
- cover the entire affected area and rinse thoroughly.
- because excessive drying of the skin may occur, start with one application daily, then gradually increase to two or two times daily if needed or as directed by a doctor.
- if bothersome dryness or peeling occurs, reduce application to once a day or every other day.
- if going outside, apply sunscreen after using this product. If irritation or sensitivity develops, stop use of both products and ask a doctor.

Other Information

Sensitivity Test for a New User. Apply product sparingly to one or two small affected areas during the first 3 days. If no discomfort occurs, follow the directions stated above. Store in controlled temperatures (4-20°C/39-68°F). Keep in a dark and dry place. Keep container tightly closed.

Inactive Ingredients

Aqua (Water), Sodium Cocoyl Isethionate, Cocamidopropyl Betaine, Glycerin, Cocamidopropyl Hydroxysultaine, Acetyl Glucosamine, Aloe Barbadensis Leaf Juice, Sodium Methyl Cocoyl Taurate, Xylitol, Xanthan Gum, Acrylates/C10-30 Alkyl Acrylate Crosspolymer, Phenoxyethanol, Sodium Benzoate, Sodium Phosphate, Sodium Citrate, Propanediol, Diethylhexyl Sodium Sulfosuccinate, Carbomer, Sodium Hydroxide.